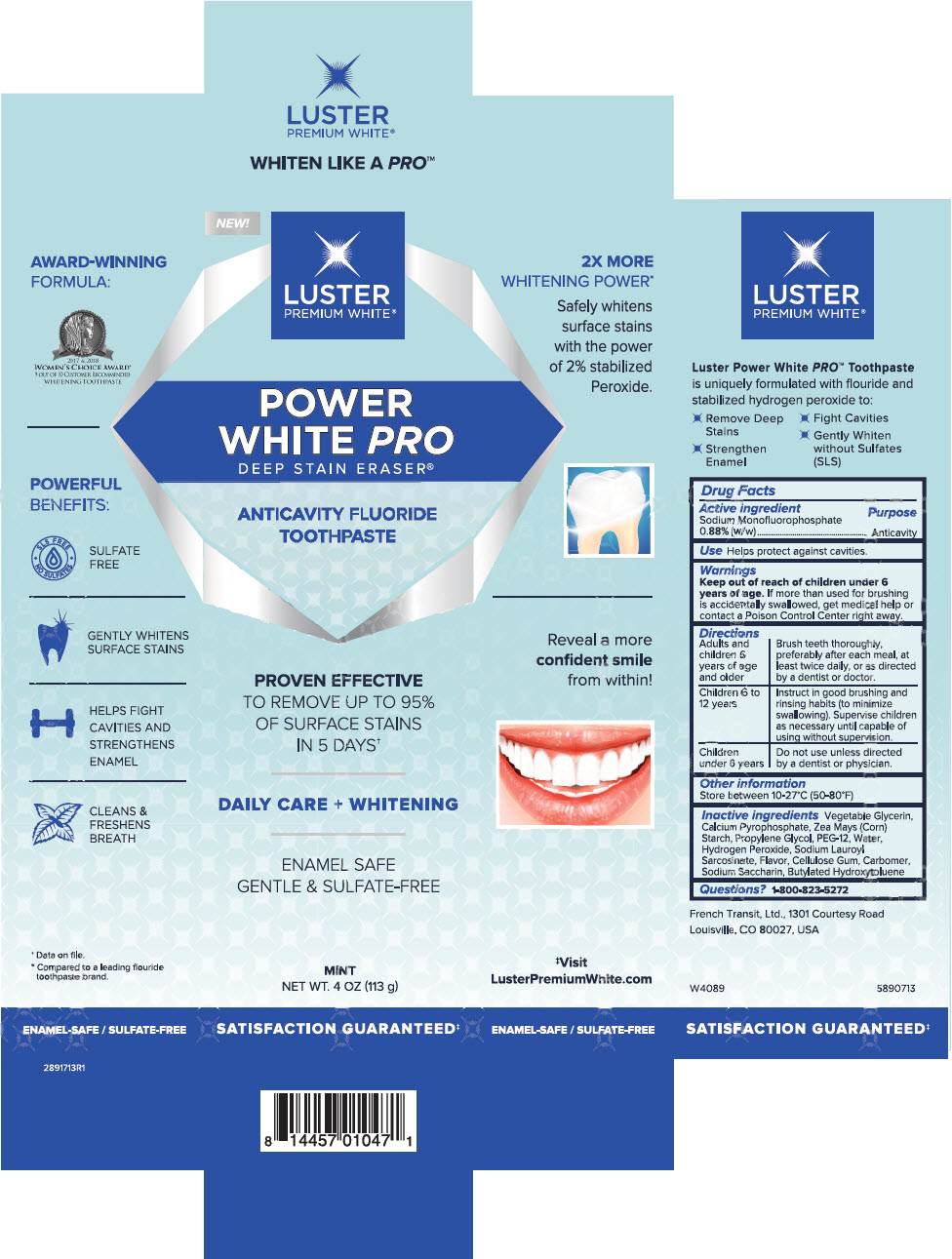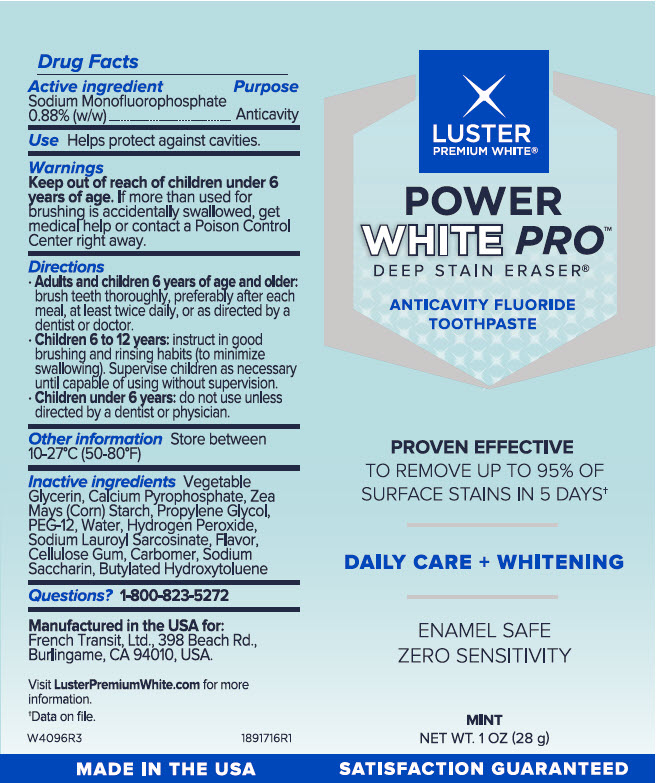 DRUG LABEL: Luster Premium White 
NDC: 72805-140 | Form: PASTE
Manufacturer: French Transit, Ltd.
Category: otc | Type: HUMAN OTC DRUG LABEL
Date: 20220112

ACTIVE INGREDIENTS: Sodium Monofluorophosphate 0.88 g/100 g
INACTIVE INGREDIENTS: Water; Calcium Pyrophosphate; STARCH, CORN; Propylene Glycol; POLYETHYLENE GLYCOL 600; Hydrogen Peroxide; Sodium Lauroyl Sarcosinate; CARBOXYMETHYLCELLULOSE SODIUM, UNSPECIFIED; CARBOMER HOMOPOLYMER TYPE A (ALLYL PENTAERYTHRITOL CROSSLINKED); SACCHARIN SODIUM; Butylated Hydroxytoluene

Luster Premium White®
Power White Pro™

Drug Facts

Active Ingredients

Sodium Monofluorophosphate 0.88% (w/w)

Purpose

Anticavity

Use

Helps protect against cavities.

Warnings

Keep out of reach of children under 6 years of age. If more than used for brushing is accidentally swallowed, get medical help or contact a Poison Control Center right away.

Directions

Adults and children 6 years of age and older

Brush teeth thoroughly, preferably after each meal, at least twice daily, or as directed by a dentist or doctor.

Children 6 to 12 years

Instruct in good brushing and rinsing habits (to minimize swallowing). Supervise children as necessary until capable of using without supervision.

Children under 6 years

Do not use unless directed by a dentist or physician

Other information

Store between 10-27 degrees Celsius (50-80 degrees Fahrenheit)

Inactive ingredients

Vegetable Glycerin, Calcium Pyrophosphate, Zea Mays (Corn) Starch, Propylene Glycol, PEG-12, Water, Hydrogen Peroxide, Sodium Lauroyl, Sarcosinate, Flavor, Cellulose Gum, Carbomer, Sodium Saccharin, Butylated Hydroxytoluene

Questions?

1-800-823-5272

PRINCIPAL DISPLAY PANEL - 113 g Tube Box

NEW!

LUSTER
PREMIUM WHITE®

POWER
WHITE PRO
DEEP STAIN ERASER®

ANTICAVITY FLUORIDE
TOOTHPASTE

PROVEN EFFECTIVE
TO REMOVE UP TO 95%
OF SURFACE STAINS
IN 5 DAYS†

DAILY CARE + WHITENING

ENAMEL SAFE
GENTLE & SULFATE-FREE

MINT
NET WT. 4 OZ (113 g)

SATISFACTION GUARANTEED‡

PRINCIPAL DISPLAY PANEL - 28 g Tube Label

LUSTER
PREMIUM WHITE®

POWER
WHITE PRO™
DEEP STAIN ERASER®

ANTICAVITY FLUORIDE
TOOTHPASTE

PROVEN EFFECTIVE
TO REMOVE UP TO 95% OF
SURFACE STAINS IN 5 DAYS†

DAILY CARE + WHITENING

ENAMEL SAFE
ZERO SENSITIVITY

MINT
NET WT. 1 OZ (28 g)

SATISFACTION GUARANTEED